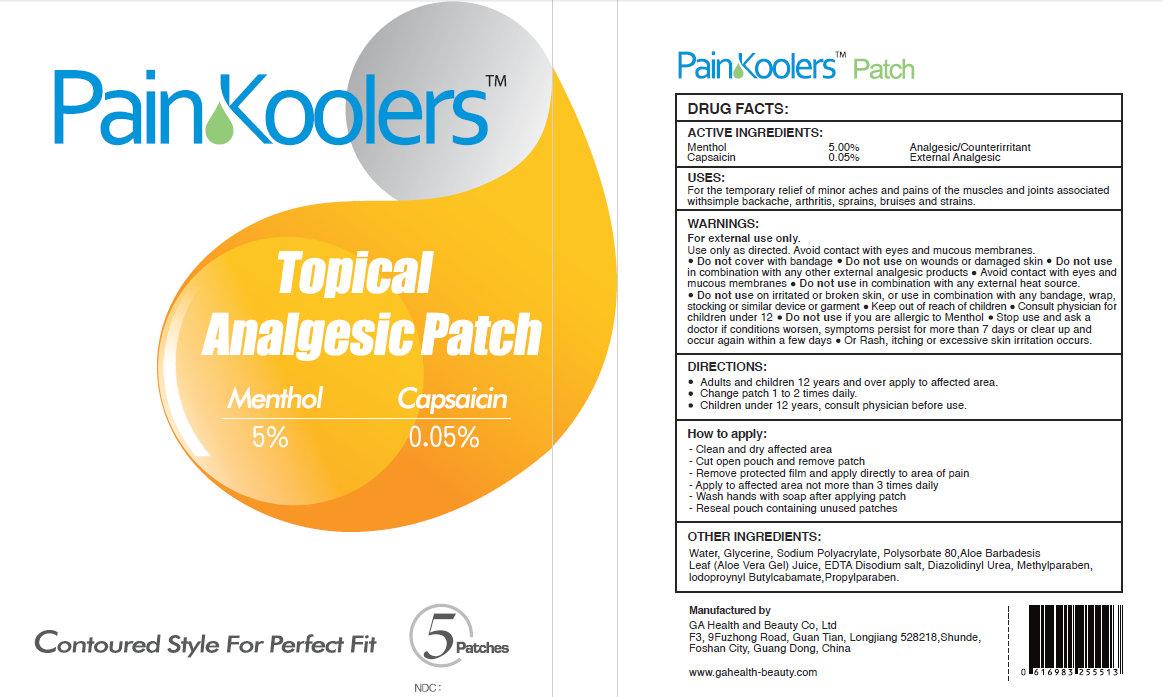 DRUG LABEL: PainKoolers Topical Analgesic Patch
NDC: 70118-001 | Form: PATCH
Manufacturer: GA Health and Beauty (FOSHAN) Co., Ltd
Category: otc | Type: HUMAN OTC DRUG LABEL
Date: 20150922

ACTIVE INGREDIENTS: MENTHOL 5 g/1 g; CAPSAICIN 0.05 g/1 g
INACTIVE INGREDIENTS: WATER; GLYCERIN; SODIUM POLYACRYLATE (2500000 MW); POLYSORBATE 80; ALOE VERA LEAF; EDETATE DISODIUM; DIAZOLIDINYL UREA; METHYLPARABEN; IODOPROPYNYL BUTYLCARBAMATE; PROPYLPARABEN

PainKoolers Topical Analgesic Patch

ACTIVE INGREDIENTS:

Menthol 5.00%
Capsaicin 0.05%

PURPOSE

Analgesic/Counterirritant
External Analgesic

USES:

For the temporary relief of minor aches and pains of the muscles and joints associated with simple backache, arthritis, sprains, bruises and strains.

WARNINGS:

For external use only.

- Use only as directed. Avoid contact with eyes and mucous membranes.
- Do not cover with bandage.
- Do not use on wounds or damaged skin.
- Do not use if you are allergic to Menthol.
- Stop use and ask a doctor if conditions worsen, symptoms persist for more than 7 days or clear up and occur again within a few days.
- Or Rash, itching or excessive skin irritation occurs.

Keep out of reach of children.

Consult Physician for children under 12.

DIRECTIONS:

- Adults and children 12 years and over apply to affected area.
- Change patch 1 to 2 times daily.
- Children under 12 years, consult physician before use.

How to apply:

Clean and dry affected area
Cut open pouch and remove patch
Remove protective film and apply directly to area of pain
Apply to affected area not more than 3 times daily
Wash hands with soap after applying patch
Reseal pouch containing unused patches

OTHER INGREDIENTS:

Water, Glycerine, Sodium Polyacrylate, Polyscorbate 80, Aloe Barbadesis Leaf (Aloe Vera Gel) Juice, EDTA Disodium salt, Diaxolidinyl Urea, Methylparaben, Iodoproynyl Butylcarbamate, Propylparaben.